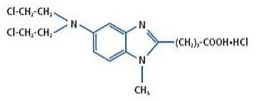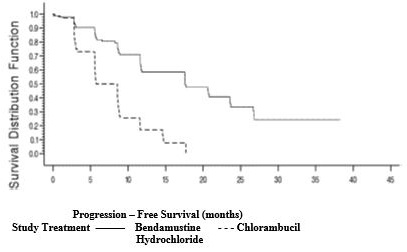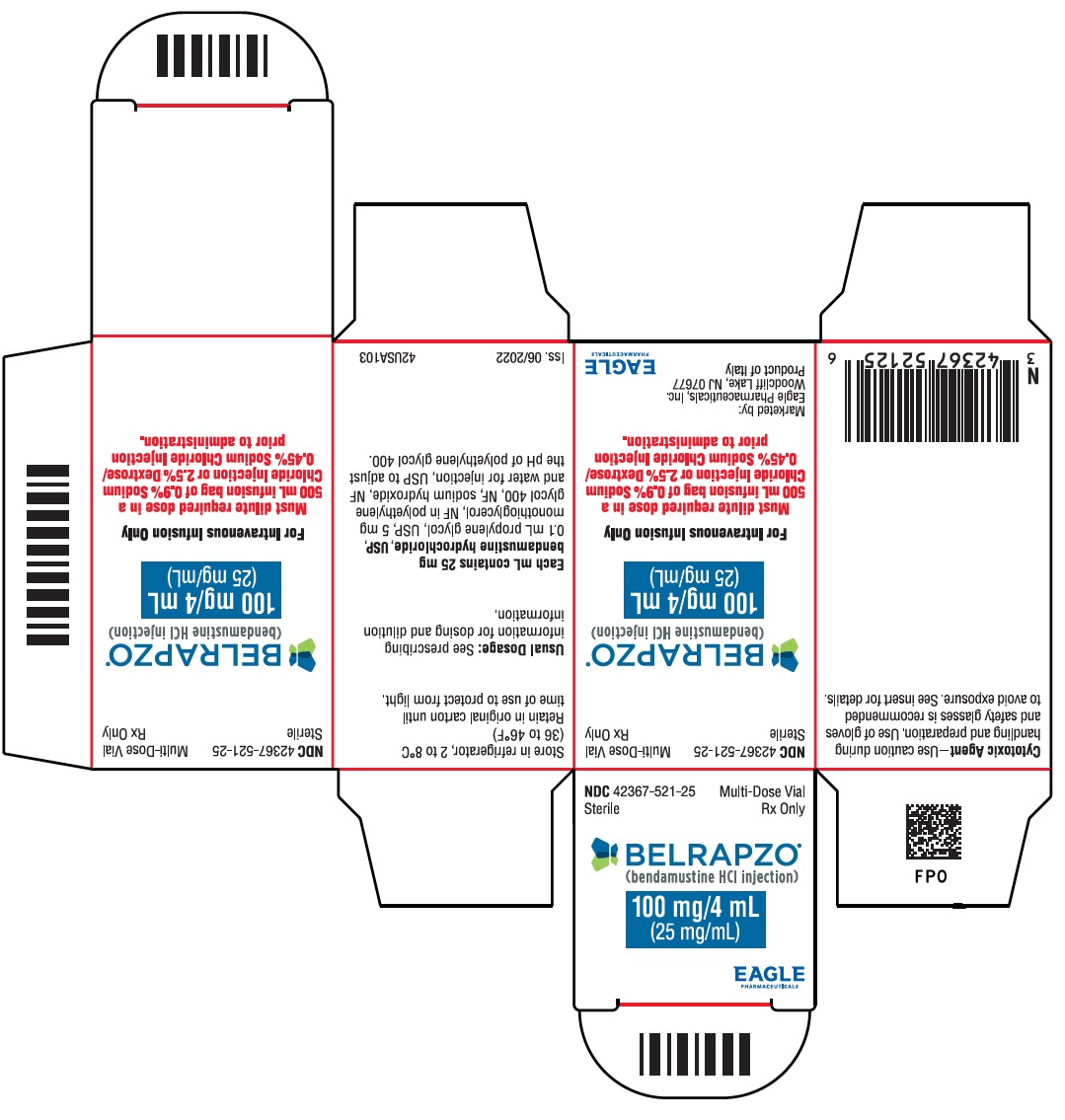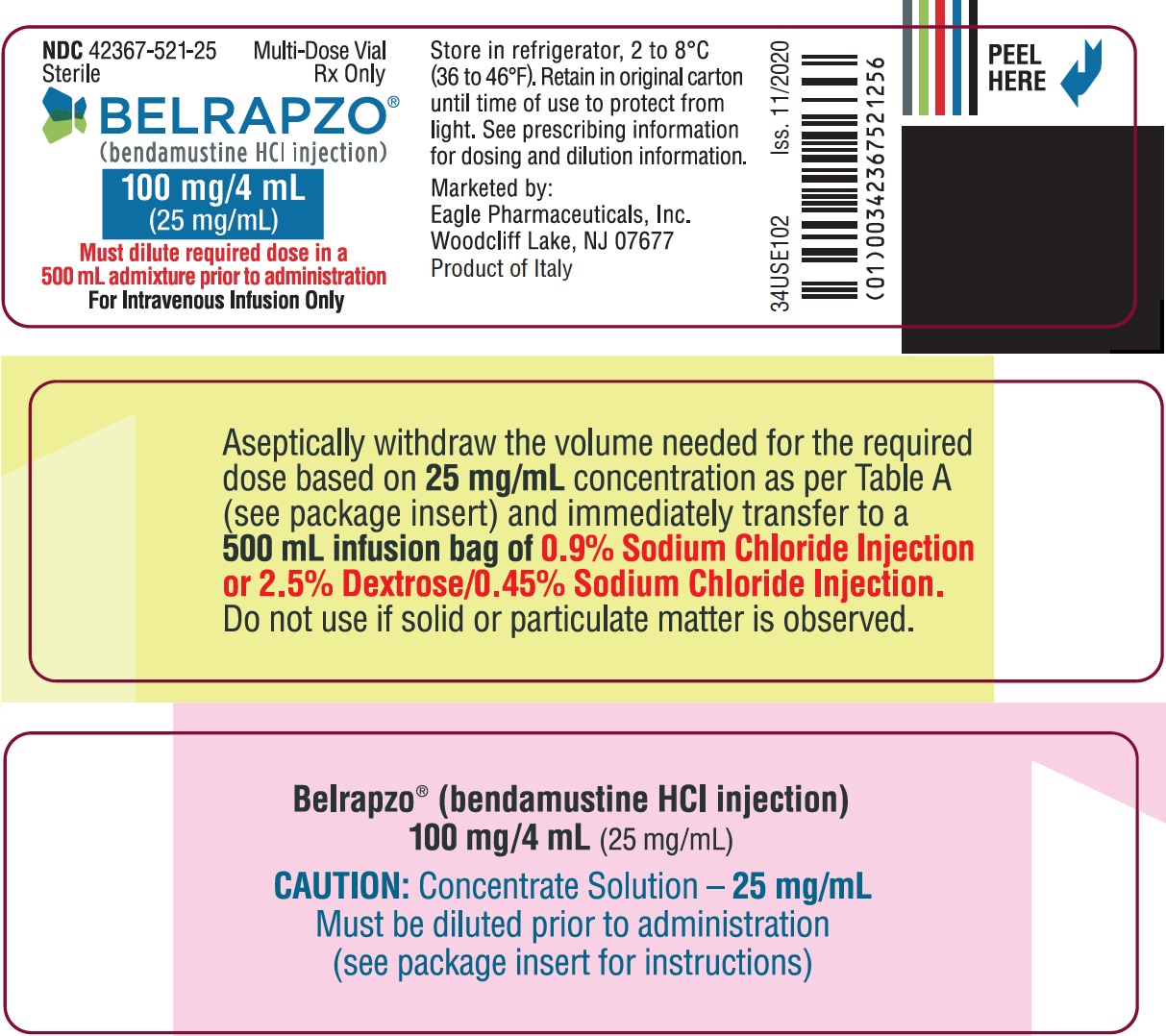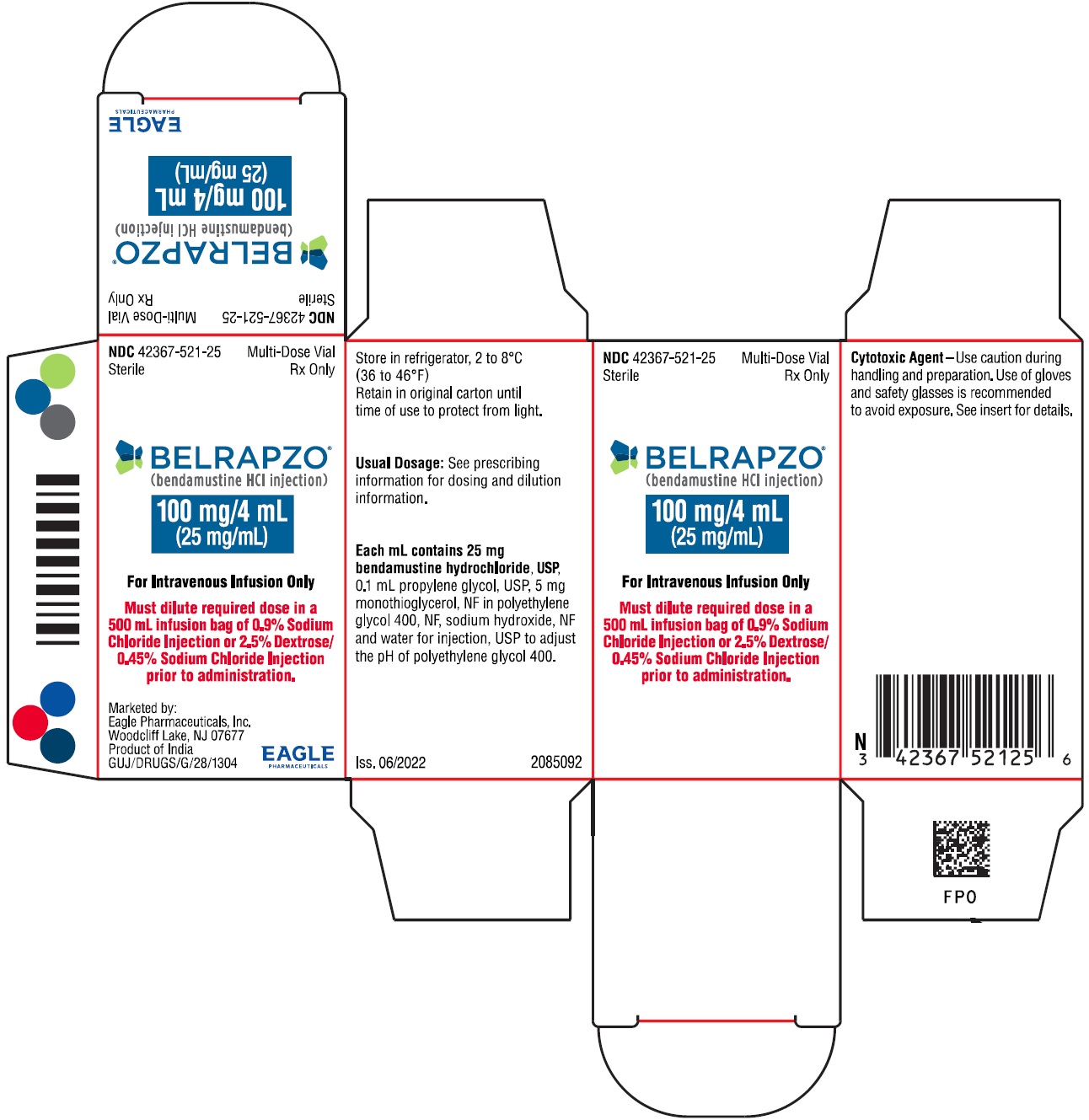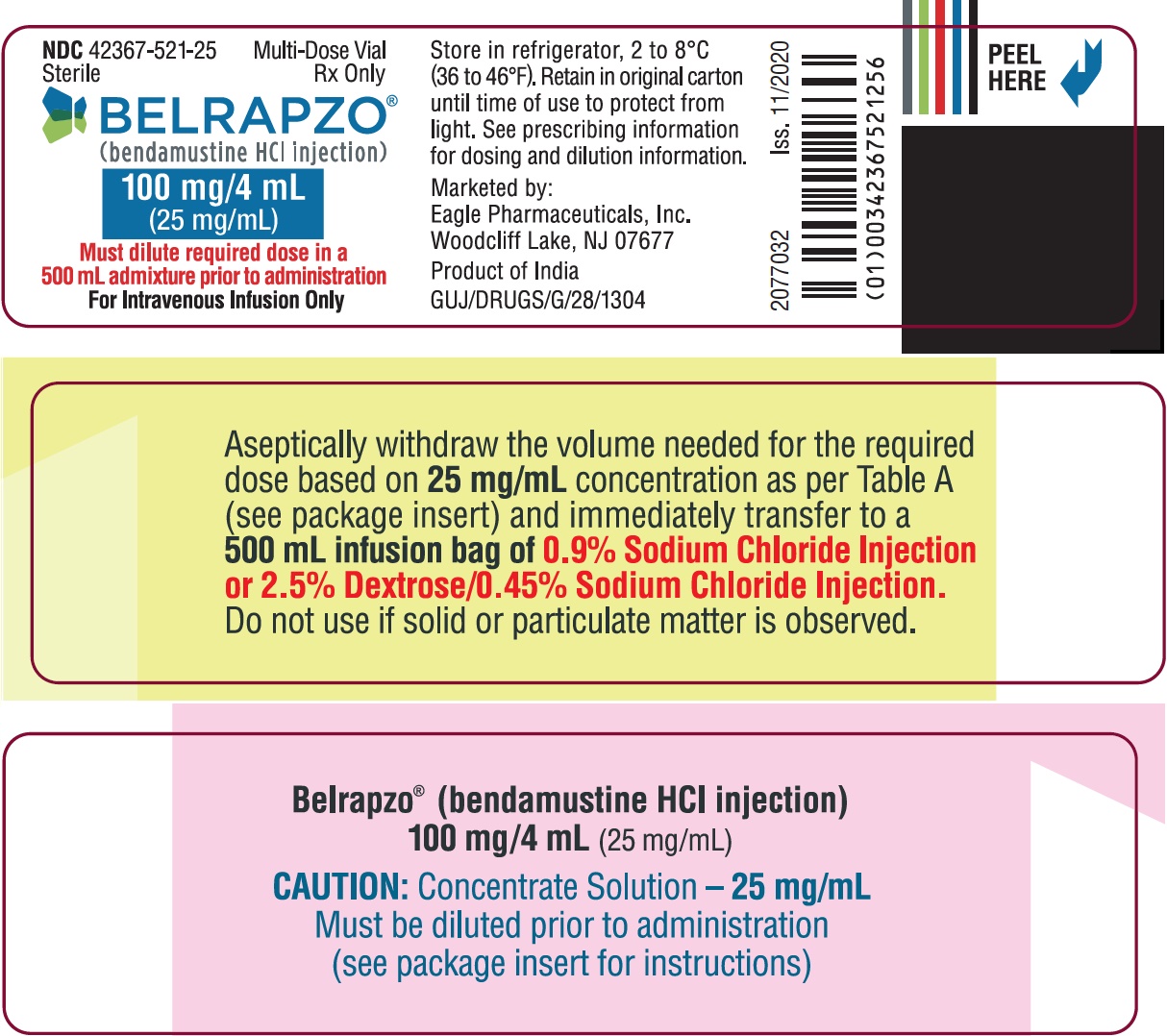 DRUG LABEL: BELRAPZO
NDC: 42367-521 | Form: INJECTION
Manufacturer: Eagle Pharmaceuticals, Inc
Category: prescription | Type: HUMAN PRESCRIPTION DRUG LABEL
Date: 20240923

ACTIVE INGREDIENTS: BENDAMUSTINE HYDROCHLORIDE 100 mg/4 mL
INACTIVE INGREDIENTS: PROPYLENE GLYCOL; MONOTHIOGLYCEROL; POLYETHYLENE GLYCOL 400; SODIUM HYDROXIDE

HIGHLIGHTS OF PRESCRIBING INFORMATION

These highlights do not include all the information needed to use BELRAPZO safely and effectively. See full prescribing information for BELRAPZO.
BELRAPZO® (bendamustine hydrochloride injection), for intravenous use.
Initial U.S. Approval: 2008

1 INDICATIONS AND USAGE

BELRAPZO is an alkylating drug indicated for treatment of patients with:

- Chronic lymphocytic leukemia (CLL). Efficacy relative to first line therapies other than chlorambucil has not been established. (1.1)
- Indolent B-cell non-Hodgkin lymphoma (NHL) that has progressed during or within six months of treatment with rituximab or a rituximab-containing regimen. (1.2)

2 DOSAGE AND ADMINISTRATION

For CLL:

- 100 mg/m^2 infused intravenously over 30 minutes on Days 1 and 2 of a 28-day cycle, up to 6 cycles. (2.1)

For NHL:

- 120 mg/m^2 infused intravenously over 60 minutes on Days 1 and 2 of a 21-day cycle, up to 8 cycles. (2.2)

3 DOSAGE FORMS AND STRENGTHS

Injection: 100 mg/4mL (25 mg/mL) in a multiple-dose vial. (3)

4 CONTRAINDICATIONS

BELRAPZO is contraindicated in patients with a history of a hypersensitivity reaction to bendamustine, polyethylene glycol 400, propylene glycol, or monothioglycerol. Reactions to bendamustine hydrochloride have included anaphylaxis and anaphylactoid reactions. (4, 5.4)

5 WARNINGS AND PRECAUTIONS

- Myelosuppression: Delay or reduce dose, and restart treatment based on ANC and platelet count recovery. (5.1)
- Infections: Monitor for fever and other signs of infection or reactivation of infections and treat promptly. (5.2)
- Progressive multifocal leukoencephalopathy (PML): Monitor for new or worsening neurological, cognitive or behavioral signs or symptoms suggestive of PML. (5.3)
- Anaphylaxis and Infusion Reactions: Severe anaphylactic reactions have occurred. Monitor clinically and discontinue drug for severe reactions. Pre-medicate in subsequent cycles for milder reactions. (5.4)
- Tumor Lysis Syndrome: May lead to acute renal failure and death; anticipate and use supportive measures in patients at high risk. (5.5)
- Skin Reactions: Discontinue for severe skin reactions. Cases of SJS, DRESS and TEN, some fatal, have been reported. (5.6)
- Hepatotoxicity: Monitor liver chemistry tests prior to and during treatment. (5.7)
- Other Malignancies: Pre-malignant and malignant diseases have been reported. (5.8)
- Extravasation Injury: Take precautions to avoid extravasation, including monitoring intravenous infusion site during and after administration. (5.9)
- Embryo-fetal toxicity: Can cause fetal harm. Advise females of reproductive potential and males with female partners of reproductive potential of the potential risk to a fetus and to use an effective method of contraception. (5.10, 8.1, 8.3)

6 ADVERSE REACTIONS

- Adverse reactions (frequency >5%) during infusion and within 24 hours post-infusion are nausea and fatigue. (6.1)
- Most common adverse reactions (≥15%) for CLL are anemia, thrombocytopenia, neutropenia, lymphopenia, leukopenia, hyperbilirubinemia, pyrexia, nausea, vomiting. (6.1, 6.2)
- Most common adverse reactions (≥15%) for NHL are lymphopenia, leukopenia, anemia, neutropenia, thrombocytopenia, nausea, fatigue, vomiting, diarrhea, pyrexia, constipation, anorexia, cough, headache, weight decreased, dyspnea, rash, and stomatitis. (6.1)

To report SUSPECTED ADVERSE REACTIONS, contact Eagle Pharmaceuticals, Inc. at 1-855-318-2170 or FDA at 1-800-FDA-1088 or http://www.fda.gov/medwatch.

7 DRUG INTERACTIONS

Consider alternative therapies that are not CYP1A2 inducers or inhibitors during treatment with BELRAPZO (7.1)

8 USE IN SPECIFIC POPULATIONS

- Lactation: Advise not to breastfeed. (8.2)
- Infertility: May impair fertility. (8.3)
- Renal Impairment: Do not use in patients with creatinine clearance < 30 mL/min. (8.6)
- Hepatic Impairment: Do not use in patients with total bilirubin 1.5-3 x ULN and AST or ALT 2.5-10 x ULN, or total bilirubin > 3 x ULN. (8.7)

FULL PRESCRIBING INFORMATION

1 INDICATIONS AND USAGE

1.1 Chronic Lymphocytic Leukemia (CLL)

BELRAPZO is indicated for the treatment of patients with chronic lymphocytic leukemia. Efficacy relative to first line therapies other than chlorambucil has not been established.

1.2 Non-Hodgkin Lymphoma (NHL)

BELRAPZO is indicated for the treatment of patients with indolent B-cell non-Hodgkin lymphoma that has progressed during or within six months of treatment with rituximab or a rituximab-containing regimen.

2 DOSAGE AND ADMINISTRATION

2.1 Dosing Instructions for CLL

Recommended Dosage:
The recommended dosage is 100 mg/m^2 administered intravenously over 30 minutes on Days 1 and 2 of a 28-day cycle, up to 6 cycles.

Dose Delays, Dosage Modifications and Reinitiation of Therapy for CLL:
Delay BELRAPZO administration in the event of Grade 4 hematologic toxicity or clinically significant Grade 2 or greater non-hematologic toxicity. Once non-hematologic toxicity has recovered to less than or equal to Grade 1 and/or the blood counts have improved [Absolute Neutrophil Count (ANC) ≥ 1 x 10^9/L, platelets ≥ 75 x 10^9/L], reinitiate BELRAPZO at the discretion of the treating physician. In addition, consider dose reduction. [see Warnings and Precautions (5.1)]

Dosage modifications for hematologic toxicity: for Grade 3 or greater toxicity, reduce the dose to 50 mg/m^2 on Days 1 and 2 of each cycle; if Grade 3 or greater toxicity recurs, reduce the dose to 25 mg/m^2 on Days 1 and 2 of each cycle.

Dosage modifications for non-hematologic toxicity: for clinically significant Grade 3 or greater toxicity, reduce the dose to 50 mg/m^2 on Days 1 and 2 of each cycle.

Consider dosage re-escalation in subsequent cycles at the discretion of the treating physician.

2.2 Dosing Instructions for NHL

Recommended Dosage:
The recommended dosage is 120 mg/m^2 administered intravenously over 60 minutes on Days 1 and 2 of a 21-day cycle, up to 8 cycles.

Dose Delays, Dosage Modifications and Reinitiation of Therapy for NHL:
Delay BELRAPZO administration in the event of a Grade 4 hematologic toxicity or clinically significant greater or equal to Grade 2 non-hematologic toxicity. Once non-hematologic toxicity has recovered to ≤ Grade 1 and/or the blood counts have improved [Absolute Neutrophil Count (ANC) ≥ 1 x 10^9/L, platelets ≥ 75 x 10^9/L], reinitiate BELRAPZO at the discretion of the treating physician. In addition, consider dose reduction. [see Warnings and Precautions (5.1)]

Dosage modifications for hematologic toxicity: for Grade 4 toxicity, reduce the dose to 90 mg/m^2 on Days 1 and 2 of each cycle; if Grade 4 toxicity recurs, reduce the dose to 60 mg/m^2 on Days 1 and 2 of each cycle.

Dosage modifications for non-hematologic toxicity: for Grade 3 or greater toxicity, reduce the dose to 90 mg/m^2 on Days 1 and 2 of each cycle; if Grade 3 or greater toxicity recurs, reduce the dose to 60 mg/m^2 on Days 1 and 2 of each cycle.

2.3 Preparation for Intravenous Administration

BELRAPZO is a hazardous drug. Follow applicable special handling and disposal procedures.1

BELRAPZO is in a multiple-dose vial. BELRAPZO is a clear and colorless to yellow solution. Store BELRAPZO at recommended refrigerated storage conditions (2° to 8°C or 36° to 46°F). When refrigerated the contents may freeze. Allow the vial to reach room temperature (15° to 30°C or 59° to 86°F) prior to use. Observe the contents of the vial for any visible solid or particulate matter. Do not use the product if solid or particulate matter is observed after reaching room temperature.

Intravenous Infusion

Aseptically withdraw the volume needed for the required dose from the 25 mg/mL solution as per Table A below and immediately transfer to a 500 mL infusion bag of one of the following diluents:
- 0.9% Sodium Chloride Injection, USP; or
- 2.5% Dextrose/0.45% Sodium Chloride Injection, USP.

The resulting final concentration of bendamustine HCl in the infusion bag should be within 0.05 to 0.7 mg/mL. After transferring, thoroughly mix the contents of the infusion bag. The admixture should be a clear and colorless to slightly yellow solution.

Use either 0.9% Sodium Chloride Injection, USP, or 2.5% Dextrose/0.45% Sodium Chloride Injection, USP, for dilution, as outlined above. No other diluents have been shown to be compatible.

Table A: Volume (mL) of BELRAPZO required for dilution into 500 mL of 0.9% Saline, or 0.45% Saline/2.5% Dextrose for a given dose (mg/m^2) and Body Surface Area (m^2)

Body Surface Area (m^2) | Volume of BELRAPZO to withdraw (mL)
Body Surface Area (m^2) | 120 mg/m^2 | 100 mg/m^2 | 90 mg/m^2 | 60 mg/m^2 | 50 mg/m^2 | 25 mg/m^2
1 | 4.8 | 4 | 3.6 | 2.4 | 2 | 1
1.1 | 5.3 | 4.4 | 4 | 2.6 | 2.2 | 1.1
1.2 | 5.8 | 4.8 | 4.3 | 2.9 | 2.4 | 1.2
1.3 | 6.2 | 5.2 | 4.7 | 3.1 | 2.6 | 1.3
1.4 | 6.7 | 5.6 | 5 | 3.4 | 2.8 | 1.4
1.5 | 7.2 | 6 | 5.4 | 3.6 | 3 | 1.5
1.6 | 7.7 | 6.4 | 5.8 | 3.8 | 3.2 | 1.6
1.7 | 8.2 | 6.8 | 6.1 | 4.1 | 3.4 | 1.7
1.8 | 8.6 | 7.2 | 6.5 | 4.3 | 3.6 | 1.8
1.9 | 9.1 | 7.6 | 6.8 | 4.6 | 3.8 | 1.9
2 | 9.6 | 8 | 7.2 | 4.8 | 4 | 2
2.1 | 10.1 | 8.4 | 7.6 | 5 | 4.2 | 2.1
2.2 | 10.6 | 8.8 | 7.9 | 5.3 | 4.4 | 2.2
2.3 | 11 | 9.2 | 8.3 | 5.5 | 4.6 | 2.3
2.4 | 11.5 | 9.6 | 8.6 | 5.8 | 4.8 | 2.4
2.5 | 12 | 10 | 9 | 6 | 5 | 2.5
2.6 | 12.5 | 10.4 | 9.4 | 6.2 | 5.2 | 2.6
2.7 | 13 | 10.8 | 9.7 | 6.5 | 5.4 | 2.7
2.8 | 13.4 | 11.2 | 10.1 | 6.7 | 5.6 | 2.8
2.9 | 13.9 | 11.6 | 10.4 | 7 | 5.8 | 2.9
3 | 14.4 | 12 | 10.8 | 7.2 | 6 | 3

Parenteral drug products should be inspected visually for particulate matter and discoloration prior to administration whenever solution and container permit. Any unused solution should be discarded according to institutional procedures for antineoplastics.

2.4 Admixture Stability

BELRAPZO contains no antimicrobial preservative. The admixture should be prepared as close as possible to the time of patient administration.

If diluted with 0.9% Sodium Chloride Injection, USP, or 2.5% Dextrose/0.45% Sodium Chloride Injection, USP, the final admixture is stable for 24 hours when stored refrigerated (2°C to 8°C or 36°F to 46°F) or for 3 hours when stored at room temperature (15°C to 30°C or 59°F to 86°F) and room light. Administration of diluted BELRAPZO must be completed within this period of time.

BELRAPZO (bendamustine hydrochloride injection) is supplied in a multiple-dose vial. Retain the partially used vial in original package to protect from light and store refrigerated (2°C to 8°C or 36°F to 46°F) if additional dose withdrawal from the same vial is intended.

2.5 Stability of Partially Used Vials (Needle Punched Vials)

BELRAPZO is supplied as a multiple-dose vial. Although it does not contain any antimicrobial preservative, BELRAPZO is bacteriostatic. The partially used vials are stable for up to 28 days when stored in its original carton under refrigeration (2°C to 8°C or 36°F to 46°F). Each vial is not recommended for more than a total of six (6) dose withdrawals.

After first use, store the partially used vial in original carton at 2°C to 8°C (36°F to 46°F), and then discard after 28 days.

3 DOSAGE FORMS AND STRENGTHS

Injection: 100 mg/4 mL (25 mg/mL) as a clear and colorless to yellow ready-to dilute solution in a multiple-dose vial.

4 CONTRAINDICATIONS

BELRAPZO is contraindicated in patients with a known hypersensitivity (e.g., anaphylactic and anaphylactoid reactions) to bendamustine, polyethylene glycol 400, propylene glycol, or monothioglycerol. [see Warnings and Precautions (5.4)]

5 WARNINGS AND PRECAUTIONS

5.1 Myelosuppression

Bendamustine hydrochloride caused severe myelosuppression (Grade 3-4) in 98% of patients in the two NHL studies [see Adverse Reactions (6.1)]. Three patients (2%) died from myelosuppression-related adverse reactions; one each from neutropenic sepsis, diffuse alveolar hemorrhage with Grade 3 thrombocytopenia, and pneumonia from an opportunistic infection (CMV).

BELRAPZO causes myelosuppression. Monitor complete blood counts, including leukocytes, platelets, hemoglobin (Hgb), and neutrophils frequently. In the clinical trials, blood counts were monitored every week initially. Hematologic nadirs were observed predominantly in the third week of therapy. Myelosuppression may require dose delays and/or subsequent dose reductions if recovery to the recommended values has not occurred by the first day of the next scheduled cycle. Prior to the initiation of the next cycle of therapy, the ANC should be ≥ 1 x 10^9/L and the platelet count should be ≥ 75 x 10^9/L. [see Dosage and Administration (2.1) and (2.2)]

5.2 Infections

Infection, including pneumonia, sepsis, septic shock, hepatitis and death has occurred in adult and pediatric patients in clinical trials and in postmarketing reports for bendamustine hydrochloride [see Adverse Reactions (6.1, 6.2)]. Patients with myelosuppression following treatment with bendamustine hydrochloride are more susceptible to infections. Advise patients with myelosuppression following BELRAPZO treatment to contact a physician immediately if they have symptoms or signs of infection.

Patients treated with BELRAPZO are at risk for reactivation of infections including (but not limited to) hepatitis B, cytomegalovirus, Mycobacterium tuberculosis, and herpes zoster. Patients should undergo appropriate measures (including clinical and laboratory monitoring, prophylaxis, and treatment) for infection and infection reactivation prior to administration.

5.3 Progressive Multifocal Leukoencephalopathy (PML)

Progressive multifocal leukoencephalopathy (PML), including fatal cases, have occurred following treatment with bendamustine, primarily in combination with rituximab or obinutuzumab [see Adverse Reactions (6.2)]. Consider PML in the differential diagnosis in patients with new or worsening neurological, cognitive or behavioral signs or symptoms. If PML is suspected, withhold BELRAPZO treatment and perform appropriate diagnostic evaluations. Consider discontinuation or reduction of any concomitant chemotherapy or immunosuppressive therapy in patients who develop PML.

5.4 Anaphylaxis and Infusion Reactions

Infusion reactions to bendamustine hydrochloride have occurred commonly in clinical trials [see Adverse Reactions (6.1)]. Symptoms include fever, chills, pruritus and rash. In rare instances severe anaphylactic and anaphylactoid reactions have occurred, particularly in the second and subsequent cycles of therapy. Monitor clinically and discontinue drug for severe reactions. Ask patients about symptoms suggestive of infusion reactions after their first cycle of therapy. Patients who experience Grade 3 or worse allergic-type reactions should not be rechallenged. Consider measures to prevent severe reactions, including antihistamines, antipyretics and corticosteroids in subsequent cycles in patients who have experienced Grade 1 or 2 infusion reactions. Discontinue BELRAPZO for patients with Grade 4 infusion reactions. Consider discontinuation for Grade 3 infusion reactions as clinically appropriate considering individual benefits, risks, and supportive care.

5.5 Tumor Lysis Syndrome

Tumor lysis syndrome associated with bendamustine hydrochloride has occurred in patients in clinical trials and in post-marketing reports [see Adverse Reactions (6.1)]. The onset tends to be within the first treatment cycle of bendamustine hydrochloride and, without intervention, may lead to acute renal failure and death. Preventive measures include vigorous hydration and close monitoring of blood chemistry, particularly potassium and uric acid levels. Allopurinol has also been used during the beginning of bendamustine hydrochloride therapy. However, there may be an increased risk of severe skin toxicity when bendamustine hydrochloride and allopurinol are administered concomitantly. [see Warnings and Precautions (5.6)]

5.6 Skin Reactions

Fatal and serious skin reactions have been reported with bendamustine hydrochloride treatment in clinical trials and postmarketing safety reports, including toxic skin reactions [Stevens-Johnson Syndrome (SJS), toxic epidermal necrolysis (TEN), and drug reaction with eosinophilia and systemic symptoms (DRESS), bullous exanthema, and rash [see Adverse Reactions (6.1 and 6.2)]. Events occurred when bendamustine hydrochloride was given as a single agent and in combination with other anticancer agents or allopurinol.

Where skin reactions occur, they may be progressive and increase in severity with further treatment. Monitor patients with skin reactions closely. If skin reactions are severe or progressive, withhold or discontinue BELRAPZO.

5.7 Hepatotoxicity

Fatal and serious cases of liver injury have been reported with bendamustine hydrochloride injection [see Adverse Reactions (6.1)]. Combination therapy, progressive disease or reactivation of hepatitis B were confounding factors in some patients. [see Warnings and Precautions (5.2)] Most cases were reported within the first three months of starting therapy. Monitor liver chemistry tests prior to and during BELRAPZO therapy.

5.8 Other Malignancies

There are reports of pre-malignant and malignant diseases that have developed in patients who have been treated with bendamustine hydrochloride, including myelodysplastic syndrome, myeloproliferative disorders, acute myeloid leukemia , bronchial carcinoma, and non-melanoma skin cancer, including basal cell carcinoma and squamous cell carcinoma [see Adverse Reactions (6.2)].

Monitor patients for the development of secondary malignancies. Perform dermatologic evaluations during and after treatment with BELRAPZO.

5.9 Extravasation Injury

Bendamustine hydrochloride extravasations have been reported in postmarketing resulting in hospitalizations from erythema, marked swelling, and pain [see Adverse Reactions (6.2)]. Assure good venous access prior to starting BELRAPZO infusion and monitor the intravenous infusion site for redness, swelling, pain, infection, and necrosis during and after administration of BELRAPZO.

5.10 Embryo-Fetal Toxicity

Based on findings from animal reproduction studies and the drug’s mechanism of action, BELRAPZO can cause fetal harm when administered to a pregnant woman. Single intraperitoneal doses of bendamustine (that approximated the maximum recommended human dose based on body surface area) to pregnant mice and rats during organogenesis caused adverse developmental outcomes, including an increase in resorptions, skeletal and visceral malformations, and decreased fetal body weights. Advise pregnant women of the potential risk to a fetus. Advise females of reproductive potential to use an effective method of contraception during treatment with BELRAPZO and for 6 months after the last dose. Advise males with female partners of reproductive potential to use effective contraception during treatment with BELRAPZO and for 3 months after the last dose. [see Use in Specific Populations (8.1, 8.3) and Clinical Pharmacology (12.1)]

6 ADVERSE REACTIONS

The following clinically significant serious adverse reactions are discussed in greater detail in other sections of the prescribing information.

- Myelosuppression [see Warnings and Precautions (5.1)]
- Infections [see Warnings and Precautions (5.2)]
- Progressive Multifocal Leukoencephalopathy [see Warnings and Precautions (5.3)]
- Anaphylaxis and Infusion Reactions[see Warnings and Precautions (5.4)]
- Tumor Lysis Syndrome [see Warnings and Precautions (5.5)]
- Skin Reactions [see Warnings and Precautions (5.6)]
- Hepatotoxicity [see Warnings and Precautions (5.7)]
- Other Malignancies [see Warnings and Precautions (5.8)]
- Extravasation Injury [see Warnings and Precautions (5.9)]

6.1 Clinical Trials Experience

Because clinical trials are conducted under widely varying conditions, adverse reaction rates observed in the clinical trials of a drug cannot be directly compared to rates in the clinical trials of another drug and may not reflect the rates observed in practice.

Clinical Trials Experience in CLL

The data described below reflect exposure to bendamustine hydrochloride in 153 patients. Bendamustine hydrochloride was studied in an active-controlled, randomized trial. The population was 45-77 years of age, 63% male, 100% white, and had treatment naïve CLL. All patients started the study at a dose of 100 mg/m^2 intravenously over 30 minutes on Days 1 and 2 every 28 days.

Adverse reactions were reported according to NCI CTC v.2.0. In the randomized CLL clinical study, non-hematologic adverse reactions (any grade) in the bendamustine hydrochloride group that occurred with a frequency greater than 15% were pyrexia (24%), nausea (20%), and vomiting (16%).

Other adverse reactions seen frequently in one or more studies included asthenia, fatigue, malaise, and weakness; dry mouth; somnolence; cough; constipation; headache; mucosal inflammation and stomatitis.

Worsening hypertension was reported in 4 patients treated with bendamustine hydrochloride in the randomized CLL clinical study and in none treated with chlorambucil. Three of these 4 adverse reactions were described as a hypertensive crisis and were managed with oral medications and resolved.

The most frequent adverse reactions leading to study withdrawal for patients receiving bendamustine hydrochloride were hypersensitivity (2%) and pyrexia (1%).

Table 1 contains the treatment emergent adverse reactions, regardless of attribution, that were reported in ≥ 5% of patients in either treatment group in the randomized CLL clinical study.

Table 1: Non-Hematologic Adverse Reactions Occurring in Randomized CLL Clinical Study in at Least 5% of Patients
 | Number (%) of patients
 | Bendamustine Hydrochloride (N=153) |  | Chlorambucil (N=143)
Body System Adverse Reaction | All Grades | Grade 3/4 | All Grades | Grade 3/4
Total number of patients with at least 1 adverse reaction | 121 (79) | 52 (34) | 96 (67) | 25 (17)
Gastrointestinal disorders
Nausea | 31 (20) | 1 (<1) | 21 (15) | 1 (<1)
Vomiting | 24 (16) | 1 (<1) | 9 (6) | 0
Diarrhea | 14 (9) | 2 (1) | 5 (3) | 0
General disorders and administration site conditions
Pyrexia | 36 (24) | 6 (4) | 8 (6) | 2 (1)
Fatigue | 14 (9) | 2 (1) | 8 (6) | 0
Asthenia | 13 (8) | 0 | 6 (4) | 0
Chills | 9 (6) | 0 | 1 (<1) | 0
Immune system disorders
Hypersensitivity | 7 (5) | 2 (1) | 3 (2) | 0
Infections and infestations
Nasopharyngitis | 10 (7) | 0 | 12 (8) | 0
Infection | 9 (6) | 3 (2) | 1 (<1) | 1 (<1)
Herpes simplex | 5 (3) | 0 | 7 (5) | 0
Investigations
Weight decreased | 11 (7) | 0 | 5 (3) | 0
Metabolism and nutrition disorders
Hyperuricemia | 11 (7) | 3 (2) | 2 (1) | 0
Respiratory, thoracic and mediastinal disorders
Cough | 6 (4) | 1 (<1) | 7 (5) | 1 (<1)
Skin and subcutaneous tissue disorders
Rash | 12 (8) | 4 (3) | 7 (5) | 3 (2)
Pruritus | 8 (5) | 0 | 2 (1) | 0

The Grade 3 and 4 hematology laboratory test values by treatment group in the randomized CLL clinical study are described in Table 2. These findings confirm the myelosuppressive effects seen in patients treated with bendamustine hydrochloride. Red blood cell transfusions were administered to 20% of patients receiving bendamustine hydrochloride compared with 6% of patients receiving chlorambucil.

Table 2: Incidence of Hematology Laboratory Abnormalities in Patients Who Received Bendamustine Hydrochloride or Chlorambucil in the Randomized CLL Clinical Study
Laboratory Abnormality | Bendamustine Hydrochloride N=150 |  | Chlorambucil N=141
Laboratory Abnormality | All Grades n (%) | Grade 3/4 n (%) | All Grades n (%) | Grade 3/4 n (%)
Hemoglobin Decreased | 134 (89) | 20 (13) | 115 (82) | 12 (9)
Platelets Decreased | 116 (77) | 16 (11) | 110 (78) | 14 (10)
Leukocytes Decreased | 92 (61) | 42 (28) | 26 (18) | 4 (3)
Lymphocytes Decreased | 102 (68) | 70 (47) | 27 (19) | 6 (4)
Neutrophils Decreased | 113 (75) | 65 (43) | 86 (61) | 30 (21)

In the randomized CLL trial, 34% of patients had bilirubin elevations, some without associated significant elevations in AST and ALT. Grade 3 or 4 increased bilirubin occurred in 3% of patients. Increases in AST and ALT of Grade 3 or 4 were limited to 1% and 3% of patients, respectively. Patients treated with bendamustine hydrochloride may also have changes in their creatinine levels. If abnormalities are detected, monitoring of these parameters should be continued to ensure that further deterioration does not occur.

Clinical Trials Experience in NHL

The data described below reflect exposure to bendamustine hydrochloride in 176 patients with indolent B-cell NHL treated in two single-arm studies. The population was 31-84 years of age, 60% male, and 40% female. The race distribution was 89% White, 7% Black, 3% Hispanic, 1% other, and <1% Asian. These patients received bendamustine hydrochloride at a dose of 120 mg/m^2 intravenously on Days 1 and 2 for up to eight 21-day cycles.

The adverse reactions occurring in at least 5% of the NHL patients, regardless of severity, are shown in Table 3. The most common non-hematologic adverse reactions (≥30%) were nausea (75%), fatigue (57%), vomiting (40%), diarrhea (37%) and pyrexia (34%). The most common non-hematologic Grade 3 or 4 adverse reactions (≥5%) were fatigue (11%), febrile neutropenia (6%), and pneumonia, hypokalemia and dehydration, each reported in 5% of patients.

Table 3: Non-Hematologic Adverse Reactions Occurring in at Least 5% of NHL Patients Treated with Bendamustine Hydrochloride by System Organ Class and Preferred Term (N=176)
Body System | Number (%) of patients*
Adverse Reaction | All Grades | Grade 3/4
Total number of patients with at least 1 adverse reaction | 176 (100) | 94 (53)
Cardiac Disorders
Tachycardia | 13 (7) | 0
Gastrointestinal disorders
Nausea | 132 (75) | 7 (4)
Vomiting | 71 (40) | 5 (3)
Diarrhea | 65 (37) | 6 (3)
Constipation | 51 (29) | 1 (<1)
Stomatitis | 27 (15) | 1 (<1)
Abdominal pain | 22 (13) | 2 (1)
Dyspepsia | 20 (11) | 0
Gastroesophageal reflux disease | 18 (10) | 0
Dry mouth | 15 (9) | 1 (<1)
Abdominal pain upper | 8 (5) | 0
Abdominal distension | 8 (5) | 0
General disorders and administration site conditions
Fatigue | 101 (57) | 19 (11)
Pyrexia | 59 (34) | 3 (2)
Chills | 24 (14) | 0
Edema peripheral | 23 (13) | 1 (<1)
Asthenia | 19 (11) | 4 (2)
Chest pain | 11 (6) | 1 (<1)
Infusion site pain | 11 (6) | 0
Pain | 10 (6) | 0
Catheter site pain | 8 (5) | 0
Infections and infestations
Herpes zoster | 18 (10) | 5 (3)
Upper respiratory tract infection | 18 (10) | 0
Urinary tract infection | 17 (10) | 4 (2)
Sinusitis | 15 (9) | 0
Pneumonia | 14 (8) | 9 (5)
Febrile neutropenia | 11 (6) | 11 (6)
Oral candidiasis | 11 (6) | 2 (1)
Nasopharyngitis | 11 (6) | 0
Investigations
Weight decreased | 31 (18) | 3 (2)
Metabolism and nutrition disorders
Anorexia | 40 (23) | 3 (2)
Dehydration | 24 (14) | 8 (5)
Decreased appetite | 22 (13) | 1 (<1)
Hypokalemia | 15 (9) | 9 (5)
Musculoskeletal and connective tissue disorders
Back pain | 25 (14) | 5 (3)
Arthralgia | 11 (6) | 0
Pain in extremity | 8 (5) | 2 (1)
Bone pain | 8 (5) | 0
Nervous system disorders
Headache | 36 (21) | 0
Dizziness | 25 (14) | 0
Dysgeusia | 13 (7) | 0
Psychiatric disorder
Insomnia | 23 (13) | 0
Anxiety | 14 (8) | 1 (<1)
Depression | 10 (6) | 0
Respiratory, thoracic and mediastinal disorders
Cough | 38 (22) | 1 (<1)
Dyspnea | 28 (16) | 3 (2)
Pharyngolaryngeal pain | 14 (8) | 1 (<1)
Wheezing | 8 (5) | 0
Nasal congestion | 8 (5) | 0
Skin and subcutaneous tissue disorders
Rash | 28 (16) | 1 (<1)
Pruritus | 11 (6) | 0
Dry skin | 9 (5) | 0
Night sweats | 9 (5) | 0
Hyperhidrosis | 8 (5) | 0
Vascular disorders
Hypotension | 10 (6) | 2 (1)
*Patients may have reported more than 1 adverse reaction.
NOTE: Patients counted only once in each preferred term category and once in each system organ class category

Hematologic toxicities, based on laboratory values and CTC grade, in NHL patients treated in both single arm studies combined are described in Table 4. Clinically important chemistry laboratory values that were new or worsened from baseline and occurred in >1% of patients at Grade 3 or 4, in NHL patients treated in both single arm studies combined were hyperglycemia (3%), elevated creatinine (2%), hyponatremia (2%), and hypocalcemia (2%).

Table 4: Incidence of Hematology Laboratory Abnormalities in Patients Who Received Bendamustine Hydrochloride in the NHL Studies
Hematology Variable | Percent of Patients
Hematology Variable | All Grades | Grade 3/4
Lymphocytes Decreased | 99 | 94
Leukocytes Decreased | 94 | 56
Hemoglobin Decreased | 88 | 11
Neutrophils Decreased | 86 | 60
Platelets Decreased | 86 | 25

In both studies, serious adverse reactions, regardless of causality, were reported in 37% of patients receiving bendamustine hydrochloride. The most common serious adverse reactions occurring in ≥5% of patients were febrile neutropenia and pneumonia. Other important serious adverse reactions reported in clinical trials and/or post-marketing experience were acute renal failure, cardiac failure, hypersensitivity, skin reactions, pulmonary fibrosis, and myelodysplastic syndrome.

Serious drug-related adverse reactions reported in clinical trials included myelosuppression, infection, pneumonia, tumor lysis syndrome and infusion reactions. Adverse reactions occurring less frequently but possibly related to bendamustine hydrochloride treatment were hemolysis, dysgeusia/taste disorder, atypical pneumonia, sepsis, herpes zoster, erythema, dermatitis, and skin necrosis.

6.2 Postmarketing Experience

The following adverse reactions have been identified during post-approval use of bendamustine hydrochloride. Because these reactions are reported voluntarily from a population of uncertain size, it is not always possible to reliably estimate their frequency or establish a causal relationship to drug exposure.

Blood and lymphatic systems disorders: Pancytopenia

Cardiovascular disorders: Atrial fibrillation, congestive heart failure (some fatal), myocardial infarction (some fatal), palpitation

General disorders and administration site conditions: Injection site reactions (including phlebitis, pruritus, irritation, pain, swelling), infusion site reactions (including phlebitis, pruritus, irritation, pain, swelling)

Immune system disorders: Anaphylaxis

Infections and infestations: Pneumocystis jirovecii pneumonia, progressive multifocal leukoencephalopathy (PML)

Renal and urinary disorders: Nephrogenic diabetes insipidus (NDI)

Respiratory, thoracic and mediastinal disorders: Pneumonitis

Skin and subcutaneous tissue disorders: Drug reaction with eosinophilia and systemic symptoms (DRESS), non-melanoma skin cancer (NMSC), Stevens-Johnson syndrome (SJS), toxic epidermal necrolysis (TEN).

7 DRUG INTERACTIONS

7.1 Effect of Other Drugs on BELRAPZO

CYP1A2 Inhibitors
The coadministration of BELRAPZO with CYP1A2 inhibitors may increase bendamustine plasma concentrations and may result in increased incidence of adverse reactions with BELRAPZO [see Clinical Pharmacology (12.3)]. Consider alternative therapies that are not CYP1A2 inhibitors during treatment with BELRAPZO.

CYP1A2 Inducers
The coadministration of BELRAPZO with CYP1A2 inducers may decrease bendamustine plasma concentrations and may result in decreased efficacy of BELRAPZO [see Clinical Pharmacology (12.3)]. Consider alternative therapies that are not CYP1A2 inducers during treatment with BELRAPZO.

8 USE IN SPECIFIC POPULATIONS

8.1 Pregnancy

Risk Summary
In animal reproduction studies, intraperitoneal administration of bendamustine to pregnant mice and rats during organogenesis at doses 0.6 to 1.8 times the maximum recommended human dose (MRHD) resulted in embryo-fetal and/or infant mortality, structural abnormalities, and alterations to growth (see Data). There are no available data on bendamustine hydrochloride use in pregnant women to evaluate for a drug-associated risk of major birth defects, miscarriage or adverse maternal or fetal outcomes. Advise pregnant women of the potential risk to a fetus.

The estimated background risk of major birth defects and miscarriage for the indicated population is unknown. All pregnancies have a background risk of birth defect, loss, or other adverse outcomes. In the U.S. general population, the estimated background risk of major birth defects and miscarriage in clinically recognized pregnancies is 2 to 4% and 15 to 20%, respectively.

Data

Animal data
Bendamustine hydrochloride was intraperitoneally administered once to mice from 210 mg/m^2 (approximately 1.8 times the MRHD) during organogenesis and caused an increase in resorptions, skeletal and visceral malformations (exencephaly, cleft palates, accessory rib, and spinal deformities) and decreased fetal body weights. This dose did not appear to be maternally toxic and lower doses were not evaluated. Repeat intraperitoneal administration of bendamustine hydrochloride in mice on gestation days 7 to 11 resulted in an increase in resorptions from 75 mg/m^2 (approximately 0.6 times the MRHD) and an increase in abnormalities from 112.5 mg/m^2 (approximately 0.9 times the MRHD), similar to those seen after a single intraperitoneal administration.

Bendamustine hydrochloride was intraperitoneally administered once to rats from 120 mg/m^2 (approximately the MRHD) on gestation days 4, 7, 9, 11, or 13 and caused embryo and fetal lethality as indicated by increased resorptions and a decrease in live fetuses. A significant increase in external (effect on tail, head, and herniation of external organs [exomphalos]) and internal (hydronephrosis and hydrocephalus) malformations were seen in dosed rats.

8.2 Lactation

Risk Summary
There are no data on the presence of bendamustine hydrochloride or its metabolites in either human or animal milk, the effects on the breastfed child, or the effects on milk production. Because of the potential for serious adverse reactions in the breastfed child, advise patients that breastfeeding is not recommended during treatment with BELRAPZO, and for 1 week after the last dose.

8.3 Females and Males of Reproductive Potential

BELRAPZO can cause embryo-fetal harm when administered to a pregnant woman [see Use in Specific Populations (8.1)].

Pregnancy Testing
Pregnancy testing is recommended for females of reproductive potential prior to initiation of treatment with BELRAPZO [see Use in Specific Populations (8.1)].

Contraception

Females
Advise female patients of reproductive potential to use effective contraception during treatment with BELRAPZO and for 6 months after the last dose.

Males
Based on genotoxicity findings, advise males with female partners of reproductive potential to use effective contraception during treatment with BELRAPZO and for 3 months after the last dose [see Nonclinical Toxicology (13.1)].

Infertility
Based on findings from clinical studies, BELRAPZO may impair male fertility. Impaired spermatogenesis, azoospermia, and total germinal aplasia have been reported in male patients treated with alkylating agents, especially in combination with other drugs. In some instances spermatogenesis may return in patients in remission, but this may occur only several years after intensive chemotherapy has been discontinued. Advise patients of the potential risk to their reproductive capacities.

Based on findings from animal studies, BELRAPZO may impair male fertility due to an increase in morphologically abnormal spermatozoa. The long-term effects of BELRAPZO on male fertility, including the reversibility of adverse effects, have not been studied [see Nonclinical Toxicology (13.1)].

8.4 Pediatric Use

Safety and effectiveness in pediatric patients have not been established.

Safety, pharmacokinetics and efficacy were assessed in a single open-label trial (NCT01088984) in patients aged 1 to 19 years with relapsed or refractory acute leukemia, including 27 patients with acute lymphocytic leukemia (ALL) and 16 patients with acute myeloid leukemia (AML). Bendamustine hydrochloride was administered as an intravenous infusion over 60 minutes on Days 1 and 2 of each 21-day cycle. There was no treatment response (CR+ CRp) in any patient. The safety profile in these patients was consistent with that seen in adults, and no new safety signals were identified.

The pharmacokinetics of bendamustine in 43 patients, aged 1 to 19 years (median age of 10 years) were within range of values previously observed in adults given the same dose based on body surface area.

8.5 Geriatric Use

No overall differences in safety were observed between patients ≥65 years of age and younger patients. Efficacy was lower in patients 65 and over with CLL receiving bendamustine hydrochloride based upon an overall response rate of 47% for patients 65 and over and 70% for younger patients. Progression free survival was also longer in younger patients with CLL receiving bendamustine (19 months vs. 12 months). No overall differences in efficacy in patients with non-Hodgkin Lymphoma were observed between geriatric patients and younger patients.

8.6 Renal Impairment

Do not use BELRAPZO in patients with creatinine clearance (CLcr) < 30 mL/min [see Clinical Pharmacology (12.3)].

8.7 Hepatic Impairment

Do not use BELRAPZO in patients with AST or ALT 2.5-10 × upper limit of normal (ULN) and total bilirubin 1.5-3 × ULN, or total bilirubin > 3 × ULN [see Clinical Pharmacology (12.3)]

10 OVERDOSAGE

The intravenous LD50 of bendamustine hydrochloride is 240 mg/m^2 in the mouse and rat. Toxicities included sedation, tremor, ataxia, convulsions and respiratory distress.

Across all clinical experience, the reported maximum single dose received was 280 mg/m^2. Three of four patients treated at this dose showed ECG changes considered dose-limiting at 7 and 21 days post-dosing. These changes included QT prolongation (one patient), sinus tachycardia (one patient), ST and T wave deviations (two patients) and left anterior fascicular block (one patient). Cardiac enzymes and ejection fractions remained normal in all patients.

No specific antidote for bendamustine hydrochloride overdose is known. Management of overdosage should include general supportive measures, including monitoring of hematologic parameters and ECGs.

11 DESCRIPTION

BELRAPZO (bendamustine hydrochloride) is an alkylating agent. The chemical name of bendamustine hydrochloride is 1H-benzimidazole-2-butanoic acid, 5-[bis(2-chloroethyl)amino]-1-methyl-, monohydrochloride. Its empirical molecular formula is C16H21Cl2N3O2 HCl, and the molecular weight is 394.7. Bendamustine hydrochloride contains a mechlorethamine group and a benzimidazole heterocyclic ring with a butyric acid substituent, and has the following structural formula:

BELRAPZO (bendamustine hydrochloride) injection for intravenous use is supplied as a sterile, clear, and colorless to yellow ready-to-dilute solution in a multiple-dose clear glass vial. Each milliliter contains 25 mg of bendamustine hydrochloride, USP, 0.1 mL of propylene glycol, USP, 5 mg of monothioglycerol, NF (used as an antioxidant) and q.s. to 1 mL polyethylene glycol 400, NF (sodium hydroxide, NF and water for injection, USP are used to prepare a 1N NaOH solution that may be used for pH modification of PEG 400).

12 CLINICAL PHARMACOLOGY

12.1 Mechanism of Action

Bendamustine is a bifunctional mechlorethamine derivative containing a purine-like benzimidazole ring. Mechlorethamine and its derivatives form electrophilic alkyl groups. These groups form covalent bonds with electron-rich nucleophilic moieties, resulting in interstrand DNA crosslinks. The bifunctional covalent linkage can lead to cell death via several pathways. Bendamustine is active against both quiescent and dividing cells. The exact mechanism of action of bendamustine remains unknown.

12.2 Pharmacodynamics

Based on the pharmacokinetics/pharmacodynamics analyses of data from adult NHL patients, nausea increased with increasing bendamustine Cmax.

Cardiac Electrophysiology
The effect of bendamustine on the QTc interval was evaluated in 53 patients with indolent NHL and mantle cell lymphoma on Day 1 of Cycle 1 after administration of rituximab at 375 mg/m^2 intravenous infusion followed by a 30-minute intravenous infusion of bendamustine at 90 mg/m^2/day. No mean changes greater than 20 milliseconds were detected up to one hour post infusion. The potential for delayed effects on the QT interval after one hour was not evaluated.

12.3 Pharmacokinetics

Absorption
Following a single IV dose of bendamustine hydrochloride Cmax typically occurred at the end of infusion. The dose proportionality of bendamustine has not been studied.

Distribution
The protein binding of bendamustine ranged from 94 to 96% and was concentration independent from 1 to 50 μg/mL. The blood to plasma concentration ratios in human blood ranged from 0.84 to 0.86 over a concentration range of 10 to 100 μg/mL.

The mean steady-state volume of distribution (Vss) of bendamustine was approximately 20 to 25 L.

Elimination
After a single intravenous dose of 120 mg/m^2 of bendamustine over 1 hour, the intermediate half-life (t½) of the parent compound is approximately 40 minutes. The mean terminal elimination t½ of two active metabolites, γ-hydroxybendamustine (M3) and N-desmethylbendamustine (M4) are approximately 3 hours and 30 minutes, respectively. Bendamustine clearance in humans is approximately 700 mL/min.

Metabolism
Bendamustine is extensively metabolized via hydrolytic, oxidative, and conjugative pathways. Bendamustine is primarily metabolized via hydrolysis to monohydroxy (HP1) and dihydroxy-bendamustine (HP2) metabolites with low cytotoxic activity in vitro. Two active minor metabolites, M3 and M4, are primarily formed via CYP1A2 in vitro. M3 and M4 concentrations of these metabolites in plasma are 1/10th and 1/100th that of the parent compound, respectively.

Excretion
Following IV infusion of radiolabeled bendamustine hydrochloride in cancer patients, approximately 76% of the dose was recovered. Approximately 50% of the dose was recovered in the urine (3.3% unchanged) and approximately 25% of the dose was recovered in the feces. Less than 1% of the dose was recovered in the urine as M3 and M4, and less than 5% of the dose was recovered in the urine as HP2.

Specific Populations
No clinically meaningful effects on the pharmacokinetics of bendamustine were observed based on age (31 to 84 years), sex, mild to moderate renal impairment (CLcr ≥ 30 mL/min), or hepatic impairment with total bilirubin 1.5 < ULN and AST or ALT < 2.5 × ULN. The effects of severe renal impairment (CLcr < 30 mL/min), or hepatic impairment with total bilirubin 1.5-3 × ULN and AST or ALT 2.5-10 × ULN or total bilirubin > 3 × ULN on the pharmacokinetics of bendamustine is unknown.

Race/Ethnicity
Exposures in Japanese subjects (n=6) were 40% higher than that in non-Japanese subjects receiving the same dose. The clinical importance of this difference on the safety and efficacy of bendamustine hydrochloride in Japanese subjects has not been established.

Drug Interaction Studies

In Vitro Studies

Effect of Bendamustine on CYP Substrates
Bendamustine did not inhibit CYP1A2, 2C9/10, 2D6, 2E1, or 3A4/5. Bendamustine did not induce metabolism of CYP1A2, CYP2A6, CYP2B6, CYP2C8, CYP2C9, CYP2C19, CYP2E1, or CYP3A4/5.

Effect of Transporters on Bendamustine Hydrochloride
Bendamustine is a substrate of P-glycoprotein and breast cancer resistance protein (BCRP).

13 NONCLINICAL TOXICOLOGY

13.1 Carcinogenesis, Mutagenesis, Impairment of Fertility

Bendamustine was carcinogenic in mice. After intraperitoneal injections at 37.5 mg/m^2/day (the lowest dose tested, approximately 0.3 times the maximum recommended human dose [MRHD]) and 75 mg/m^2/day (approximately 0.6 times the MRHD) for 4 days, peritoneal sarcomas in female AB/jena mice were produced. Oral administration at 187.5 mg/m^2/day (the only dose tested, approximately 1.6 times the MRHD) for 4 days induced mammary carcinomas and pulmonary adenomas.

Bendamustine is a mutagen and clastogen. In a reverse bacterial mutation assay (Ames assay), bendamustine was shown to increase revertant frequency in the absence and presence of metabolic activation. Bendamustine was clastogenic in human lymphocytes in vitro, and in rat bone marrow cells in vivo (increase in micronucleated polychromatic erythrocytes) from 37.5 mg/m^2, (the lowest dose tested, approximately 0.3 times the MRHD).

Bendamustine induced morphologic abnormalities in spermatozoa in mice. Following tail vein injection of bendamustine at 120 mg/m^2 or a saline control on days 1 and 2 for a total of three weeks, the number of spermatozoa with morphologic abnormalities was 16% higher in the bendamustine-treated group as compared to the saline control group.

14 CLINICAL STUDIES

14.1 Chronic Lymphocytic Leukemia (CLL)

The safety and efficacy of bendamustine hydrochloride were evaluated in an open-label, randomized, controlled multicenter trial comparing bendamustine hydrochloride to chlorambucil. The trial was conducted in 301 previously-untreated patients with Binet Stage B or C (Rai Stages I - IV) CLL requiring treatment. Need-to-treat criteria included hematopoietic insufficiency, B-symptoms, rapidly progressive disease or risk of complications from bulky lymphadenopathy. Patients with autoimmune hemolytic anemia or autoimmune thrombocytopenia, Richter’s syndrome, or transformation to prolymphocytic leukemia were excluded from the study.

The patient populations in the bendamustine hydrochloride and chlorambucil treatment groups were balanced with regard to the following baseline characteristics: age (median 63 vs. 66 years), gender (63% vs. 61% male), Binet stage (71% vs. 69% Binet B), lymphadenopathy (79% vs. 82%), enlarged spleen (76% vs. 80%), enlarged liver (48% vs. 46%), hypercellular bone marrow (79% vs. 73%), “B” symptoms (51% vs. 53%), lymphocyte count (mean 65.7x10^9/L vs. 65.1x10^9/L), and serum lactate dehydrogenase concentration (mean 370.2 vs. 388.4 U/L). Ninety percent of patients in both treatment groups had immuno-phenotypic confirmation of CLL (CD5, CD23 and either CD19 or CD20 or both).

Patients were randomly assigned to receive either bendamustine hydrochloride at 100 mg/m^2, administered intravenously over a period of 30 minutes on Days 1 and 2 or chlorambucil at 0.8 mg/kg (Broca’s normal weight) administered orally on Days 1 and 15 of each 28-day cycle. Efficacy endpoints of objective response rate and progression-free survival were calculated using a pre-specified algorithm based on NCI working group criteria for CLL.

The results of this open-label randomized study demonstrated a higher rate of overall response and a longer progression-free survival for bendamustine hydrochloride compared to chlorambucil (see Table 5). Survival data are not mature.

Table 5: Efficacy Data for CLL
 | Bendamustine Hydrochloride (N=153) | Chlorambucil (N=148) | p-value
Response Rate n (%)
Overall response rate | 90 (59) | 38 (26) | <0.0001
(95% CI) | (51, 66.6) | (18.6, 32.7)
Complete response (CR)* | 13 (8) | 1 (<1)
Nodular partial response (nPR)** | 4 (3) | 0
Partial response (PR) † | 73 (48) | 37 (25)
Progression-Free Survival ††
Median, months (95% CI) | 18 (11.7, 23.5) | 6 (5.6, 8.6)
Hazard ratio (95% CI) | 0.27 (0.17, 0.43) |  | <0.0001
CI = confidence interval
* CR was defined as peripheral lymphocyte count ≤ 4 x 10^9/L, neutrophils ≥ 1.5 x 10^9/L, platelets >100 x 10^9/L, hemoglobin > 110g/L, without transfusions, absence of palpable hepatosplenomegaly, lymph nodes ≤ 1.5 cm, < 30% lymphocytes without nodularity in at least a normocellular bone marrow and absence of “B” symptoms. The clinical and laboratory criteria were required to be maintained for a period of at least 56 days.
** nPR was defined as described for CR with the exception that the bone marrow biopsy shows persistent nodules.
† PR was defined as ≥50% decrease in peripheral lymphocyte count from the pretreatment baseline value, and either ≥50% reduction in lymphadenopathy, or ≥50% reduction in the size of spleen or liver, as well as one of the following hematologic improvements: neutrophils ≥ 1.5 x 10^9/L or 50% improvement over baseline, platelets >100 x 10^9/L or 50% improvement over baseline, hemoglobin >110g/L or 50% improvement over baseline without transfusions, for a period of at least 56 days.
†† PFS was defined as time from randomization to progression or death from any cause.

Kaplan-Meier estimates of progression-free survival comparing bendamustine hydrochloride with chlorambucil are shown in Figure 1.

Figure 1. Progression-Free Survival

14.2 Non-Hodgkin Lymphoma (NHL)

The efficacy of bendamustine hydrochloride was evaluated in a single arm study of 100 patients with indolent B-cell NHL that had progressed during or within six months of treatment with rituximab or a rituximab-containing regimen. Patients were included if they relapsed within 6 months of either the first dose (monotherapy) or last dose (maintenance regimen or combination therapy) of rituximab. All patients received bendamustine hydrochloride intravenously at a dose of 120 mg/m^2, on Days 1 and 2 of a 21-day treatment cycle. Patients were treated for up to 8 cycles.

The median age was 60 years, 65% were male, and 95% had a baseline WHO performance status of 0 or 1. Major tumor subtypes were follicular lymphoma (62%), diffuse small lymphocytic lymphoma (21%), and marginal zone lymphoma (16%). Ninety-nine percent of patients had received previous chemotherapy, 91% of patients had received previous alkylator therapy, and 97% of patients had relapsed within 6 months of either the first dose (monotherapy) or last dose (maintenance regimen or combination therapy) of rituximab.

Efficacy was based on the assessments by a blinded independent review committee (IRC) and included overall response rate (complete response + complete response unconfirmed + partial response) and duration of response (DR) as summarized in Table 6.

Table 6: Efficacy Data for NHL*
 | Bendamustine Hydrochloride (N=100)
Response Rate (%)
Overall response rate (CR+CRu+PR) | 74
(95% CI) | (64.3, 82.3)
Complete response (CR) | 13
Complete response unconfirmed (CRu) | 4
Partial response (PR) | 57
Duration of Response (DR)
Median, months (95% CI) | 9.2 months (7.1, 10.8)
CI = confidence interval
*IRC assessment was based on modified International Working Group response criteria (IWG-RC). Modifications to IWG-RC specified that a persistently positive bone marrow in patients who met all other criteria for CR would be scored as PR. Bone marrow sample lengths were not required to be ≥20 mm

15 REFERENCES

1. OSHA Hazardous Drugs. OSHA. [http://www.osha.gov/SLTC/hazardousdrugs/index.html]

16 HOW SUPPLIED/STORAGE AND HANDLING

Safe Handling and Disposal
BELRAPZO (bendamustine hydrochloride) is a hazardous drug. Follow applicable special handling and disposal procedures^1. Care should be exercised in the handling and preparation of solutions prepared from BELRAPZO. The use of gloves and safety glasses is recommended to avoid exposure in case of breakage of the vial or other accidental spillage. If gloves come in contact with BELRAPZO prior to dilution, remove gloves and follow disposal procedures^1. If a solution of BELRAPZO (bendamustine hydrochloride) contacts the skin, wash the skin immediately and thoroughly with soap and water. If BELRAPZO (bendamustine hydrochloride) contacts the mucous membranes, flush thoroughly with water.

How Supplied
BELRAPZO (bendamustine hydrochloride) is supplied in individual cartons of 5 mL clear multiple-dose vials containing 100 mg of bendamustine hydrochloride as a clear, and colorless to yellow ready-to-dilute solution.

NDC 42367-521-25, 100 mg/4 mL (25 mg/mL).

Storage
Store BELRAPZO (bendamustine hydrochloride) in refrigerator, 2°C to 8°C (36°C to 46°F). Retain in original carton until time of use to protect from light.

17 PATIENT COUNSELING INFORMATION

Myelosuppression
Inform patients of the likelihood that BELRAPZO will cause a decrease in white blood cells, platelets, and red blood cells and the need for frequent monitoring of blood counts. Advise patients to report shortness of breath, significant fatigue, bleeding, fever, or other signs of infection. [see Warnings and Precautions (5.1)]

Progressive Multifocal Leukoencephalopathy (PML)
Inform patients to immediately contact their healthcare provider if they experience confusion, memory loss, trouble thinking, difficulty talking or walking, vision loss or other neurological or cognitive symptoms [see Warnings and Precautions (5.3)].

Anaphylaxis and Infusion Reactions
Inform patients of the possibility of serious or mild allergic reactions and to immediately report rash, facial swelling, or difficulty breathing during or soon after infusion. [see Warnings and Precautions (5.4)].

Skin Reactions
Advise patients that a rash or itching may occur during treatment with BELRAPZO. Advise patients to immediately report severe or worsening rash or itching. [see Warnings and Precautions (5.6)].

Hepatotoxicity
Inform patients of the possibility of developing liver function abnormalities and serious hepatic toxicity. Advise patients to immediately contact their health care provider if signs of liver failure occur, including jaundice, anorexia, bleeding or bruising. [see Warnings and Precautions (5.7)].

Fatigue
Advise patients that BELRAPZO may cause tiredness and to avoid driving any vehicle or operating any dangerous tools or machinery if they experience this side effect. [see Adverse Reactions (6.1)]

Nausea and Vomiting
Advise patients that BELRAPZO may cause nausea and/or vomiting. Patients should report nausea and vomiting so that symptomatic treatment may be provided. [see Adverse Reactions (6.1)]

Diarrhea
Advise patients that BELRAPZO may cause diarrhea. Patients should report diarrhea to the physician so that symptomatic treatment may be provided. [see Adverse Reactions (6.1)]

Non-melanoma Skin Cancer (NMSC)
Advise patients to undergo regular skin cancer screenings, and to report any suspicious skin changes to their healthcare provider [see Warnings and Precautions (5.8)]

Embryo-Fetal Toxicity
Advise pregnant women and females of reproductive potential of the potential risk to a fetus. Advise females to inform their healthcare provider of a known or suspected pregnancy [see Warnings and Precautions (5.10), Use in Specific Populations (8.1, 8.3), and Nonclinical Toxicology (13.1)]. Advise female patients of reproductive potential to use effective contraception during treatment with BELRAPZO and for 6 months after the last dose [see Use in Specific Populations (8.1, 8.3)]. Advise males with female partners of reproductive potential to use effective contraception during treatment with BELRAPZO and for 3 months after the last dose [see Use in Specific Populations (8.3), and Nonclinical Toxicology (13.1)].

Lactation
Advise females not to breastfeed during treatment with BELRAPZO and for 1 week after the last dose [see Use in Specific Populations (8.2)].

Infertility
Advise males of reproductive potential that BELRAPZO may impair fertility [see Use in Specific Populations (8.3)].

Marketed by
Eagle Pharmaceuticals, Inc.
50 Tice Boulevard, Suite 315
Woodcliff Lake, NJ

All rights reserved.